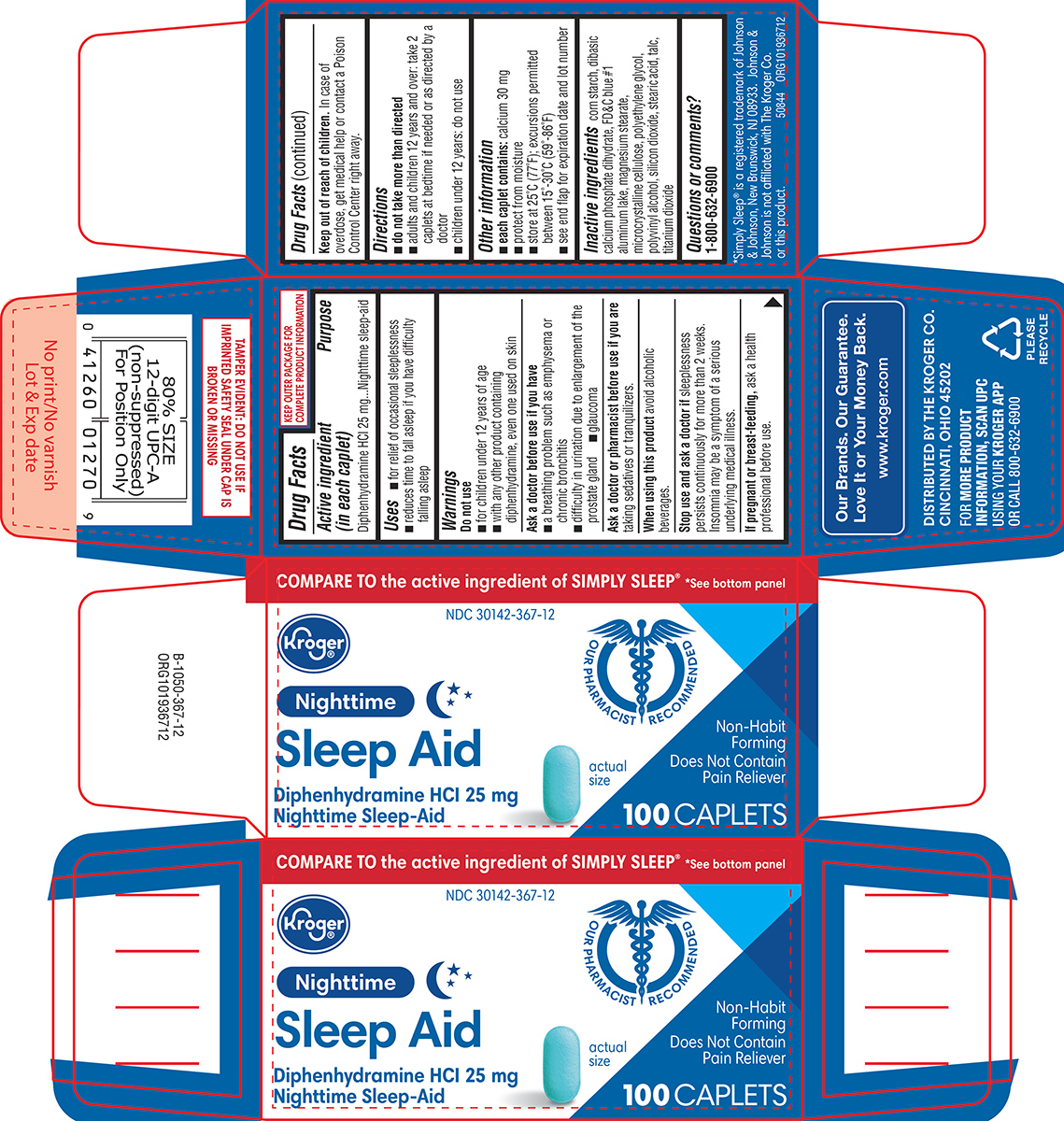 DRUG LABEL: Sleep Aid
NDC: 30142-367 | Form: TABLET, FILM COATED
Manufacturer: Kroger Company
Category: otc | Type: HUMAN OTC DRUG LABEL
Date: 20260122

ACTIVE INGREDIENTS: DIPHENHYDRAMINE HYDROCHLORIDE 25 mg/1 1
INACTIVE INGREDIENTS: STARCH, CORN; DIBASIC CALCIUM PHOSPHATE DIHYDRATE; FD&C BLUE NO. 1 ALUMINUM LAKE; MAGNESIUM STEARATE; MICROCRYSTALLINE CELLULOSE; POLYETHYLENE GLYCOL, UNSPECIFIED; POLYVINYL ALCOHOL, UNSPECIFIED; SILICON DIOXIDE; STEARIC ACID; TALC; TITANIUM DIOXIDE

Kroger 44-367-Delisted

Active ingredient (in each caplet)

Diphenhydramine HCl 25 mg

Purpose

Nighttime sleep-aid

Uses

- for relief of occasional sleeplessness
- reduces time to fall asleep if you have difficulty falling asleep

Warnings

Do not use

- for children under 12 years of age
- with any other product containing diphenhydramine, even one used on skin

Ask a doctor before use if you have

- a breathing problem such as emphysema or chronic bronchitis
- glaucoma
- difficulty in urination due to enlargement of the prostate gland

Ask a doctor or pharmacist before use if you are

taking sedatives or tranquilizers.

When using this product

avoid alcoholic beverages.

Stop use and ask a doctor if

sleeplessness persists continuously for more than 2 weeks. Insomnia may be a symptom of a serious underlying medical illness.

If pregnant or breast-feeding,

ask a health professional before use.

Keep out of reach of children.

In case of overdose, get medical help or contact a Poison Control Center right away.

Directions

- do not take more than directed
- adults and children 12 years and over: take 2 caplets at bedtime if needed or as directed by a doctor
- children under 12 years: do not use

Other information

- each caplet contains: calcium 30 mg
- protect from moisture
- store at 25ºC (77ºF); excursions permitted between 15°-30°C (59°-86°F)
- see end flap for expiration date and lot number

Inactive ingredients

corn starch, dibasic calcium phosphate dihydrate, FD&C blue #1 aluminum lake, magnesium stearate, microcrystalline cellulose, polyethylene glycol, polyvinyl alcohol, silicon dioxide, stearic acid, talc, titanium dioxide

Questions or comments?

1-800-632-6900

Principal Display Panel

COMPARE TO the active ingredient of SIMPLY SLEEP® *See bottom panel

NDC 30142-367-12

Kroger®

Nighttime
Sleep Aid
Diphenhydramine HCI 25 mg
Nighttime Sleep-Aid

Non-Habit
Forming
Does Not Contain
Pain Reliever

actual
size

100 CAPLETS

OUR PHARMACIST
RECOMMENDED

TAMPER EVIDENT: DO NOT USE IF
IMPRINTED SAFETY SEAL UNDER CAP IS
BROKEN OR MISSING

*Simply Sleep® is a registered trademark of Johnson
& Johnson, New Brunswick, NJ 08933. Johnson &
Johnson is not affiliated with The Kroger Co.
or this product.

50844 ORG101936712

Our Brands. Our Guarantee.
Love It or Your Money Back.
www.kroger.com

DISTRIBUTED BY THE KROGER CO.
CINCINNATI, OHIO 45202

FOR MORE PRODUCT
INFORMATION, SCAN UPC
USING YOUR KROGER APP
OR CALL 800-632-6900

PLEASE
RECYCLE

44-367